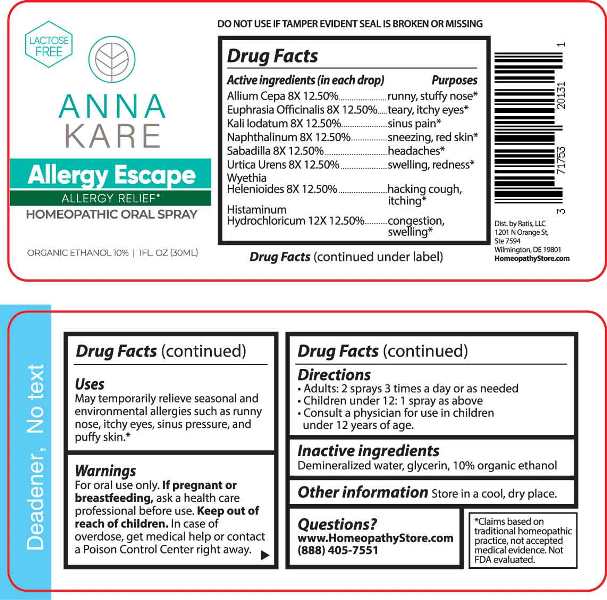 DRUG LABEL: Allergy Escape
NDC: 71753-2013 | Form: SPRAY
Manufacturer: Ratis, LLC
Category: homeopathic | Type: HUMAN OTC DRUG LABEL
Date: 20230712

ACTIVE INGREDIENTS: ONION 8 [hp_X]/1 mL; EUPHRASIA STRICTA 8 [hp_X]/1 mL; POTASSIUM IODIDE 8 [hp_X]/1 mL; NAPHTHALENE 8 [hp_X]/1 mL; SCHOENOCAULON OFFICINALE SEED 8 [hp_X]/1 mL; URTICA URENS WHOLE 8 [hp_X]/1 mL; WYETHIA HELENIOIDES ROOT 8 [hp_X]/1 mL; HISTAMINE DIHYDROCHLORIDE 12 [hp_X]/1 mL
INACTIVE INGREDIENTS: WATER; GLYCERIN; ALCOHOL

DRUG FACTS:

ACTIVE INGREDIENTS:

(in each drop) Allium Cepa 8X 12.50%, Euphrasia Officinalis 8X 12.50%, Kali Iodatum 8X 12.50%, Naphthalinum 8X 12.50%, Sabadilla 8X 12.50%, Urtica Urens 8X 12.50%, Wyethia Helenioides 8X 12.50%, Histaminum Hydrochloricum 12X 12.50%.

PURPOSES:

Allium Cepa – runny, stuffy nose,* Euphrasia Officinalis – teary, itchy eyes,* Kali Iodatum – sinus pain,* Naphthalinum – sneezing, red skin,* Sabadilla - headaches,* Urtica Urens – swelling, redness,* Wyethia Helenioides – hacking cough, itching,* Histaminum Hydrochloricum – congestion, swelling.*

USES:

May temporarily relieve seasonal and environmental allergies such as runny nose, itchy eyes, sinus pressure, and puffy skin.*

* Claims based on traditional homeopathic practice, not accepted medical evidence. Not FDA evaluated.

WARNINGS:

For oral use only. If pregnant or breast-feeding, ask a health care professional before use.

Keep out of reach of children. In case of overdose, get medical help or contact a Poison Control center right away.

DO NOT USE IF TAMPER EVIDENT SEAL IS BROKEN OR MISSING

KEEP OUT OF REACH OF CHILDREN:

In case of overdose, get medical help or contact a Poison Control center right away.

DIRECTIONS:

• Adults: 2 sprays 3 times a day or as needed

• Children under 12: 1 spray as above

• Consult a physician for use in children under 12 years of age.

Store in a cool, dry place

INACTIVE INGREDIENTS:

Demineralized water, glycerin, 10% organic ethanol

QUESTIONS:

www.HomeopathyStore.com

(888) 405-7551

Dist. by Ratis, LLC

1201 N Orange St,

Ste 7594

Wilmington, DE 19801

PACKAGE LABLE DISPLAY:

LACTOSE FREE

ANNA

KARE

Allergy Escape

ALLERGY RELIEF*

HOMEOPATHIC ORAL SPRAY

1FL. OZ (30ML)